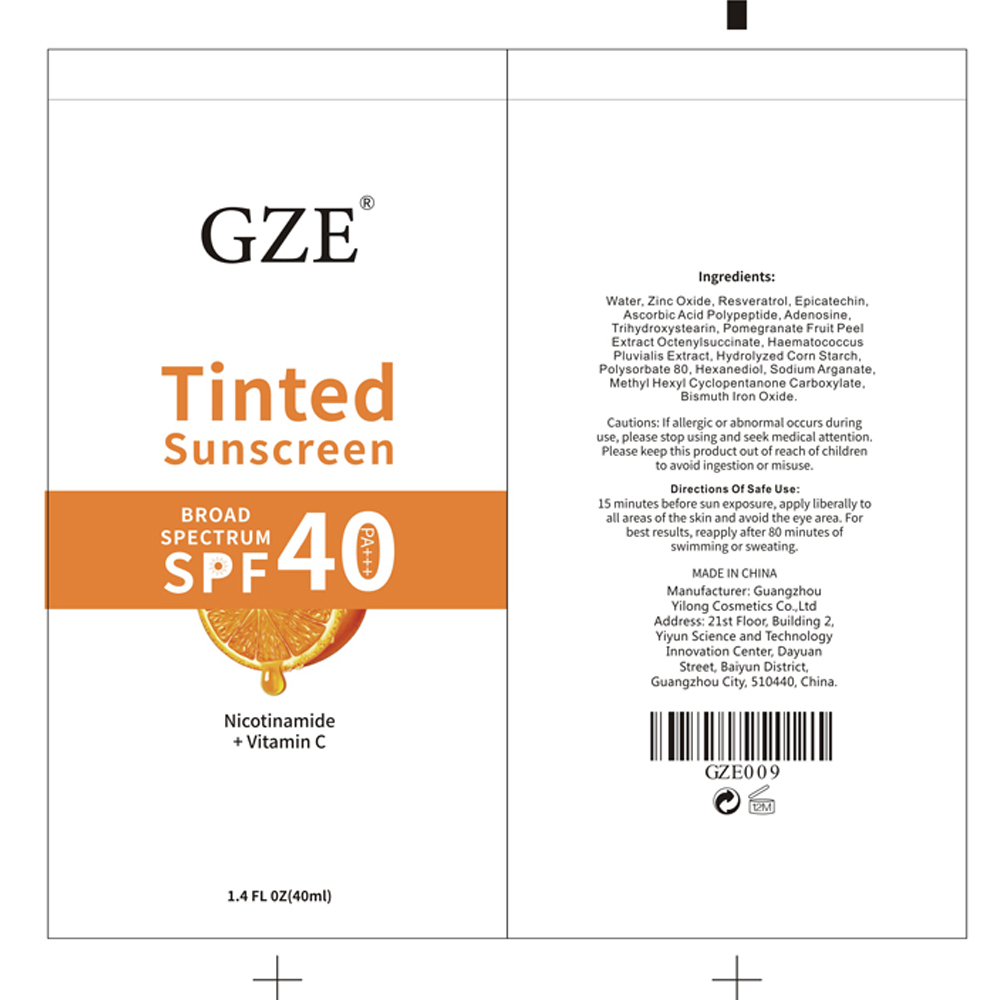 DRUG LABEL: GZE Tinted Sunscreen
NDC: 74458-009 | Form: LOTION
Manufacturer: Guangzhou Yilong Cosmetics Co., Ltd
Category: otc | Type: HUMAN OTC DRUG LABEL
Date: 20241018

ACTIVE INGREDIENTS: ZINC OXIDE 15 g/100 mL
INACTIVE INGREDIENTS: ASCORBIC ACID; HEXANEDIOL; WATER; RESVERATROL; EPICATECHIN; HAEMATOCOCCUS PLUVIALIS; STARCH, CORN; ADENOSINE; TRIHYDROXYSTEARIN; POLYSORBATE 80; POMEGRANATE; METHYL HEXYL CYCLOPENTANONE CARBOXYLATE

GZE Tinted Sunscreen

INACTIVE INGREDIENT

Water

Resveratrol

Epicatechin

Ascorbic Acid Polypeptide

Adenosine

Trihydroxystearin

Pomegranate Fruit Peel Extract Octenylsuccinate

Haematococcus Pluvialis Extract

Hydrolyzed Corn Starch

Polysorbate 80

Hexanediol

Sodium Arganate

Methyl Hexyl Cyclopentanone Carboxylate

Bismuth Iron Oxide

ACTIVE INGREDIENT

Zinc Oxide

PURPOSE

Sunscreen.

INDICATIONS AND USAGE

Apply full body sunscreen ahead of time, avoiding the eye area, for the first fifteen minutes of exposure to the sun.

WARNINGS

For external use only.

Stop use and ask a doctor if rash occurs.

Do not use on damaged or broken skin.

When using this product keep out of eyes. Rinse with water to remove.

Keep out of reach of children. If swallowed, get medical help or contact a Poison Control Center right away.

DOSAGE AND ADMINISTRATION

Apply full body sunscreen ahead of time, avoiding the eye area, for the first fifteen minutes of exposure to the sun.